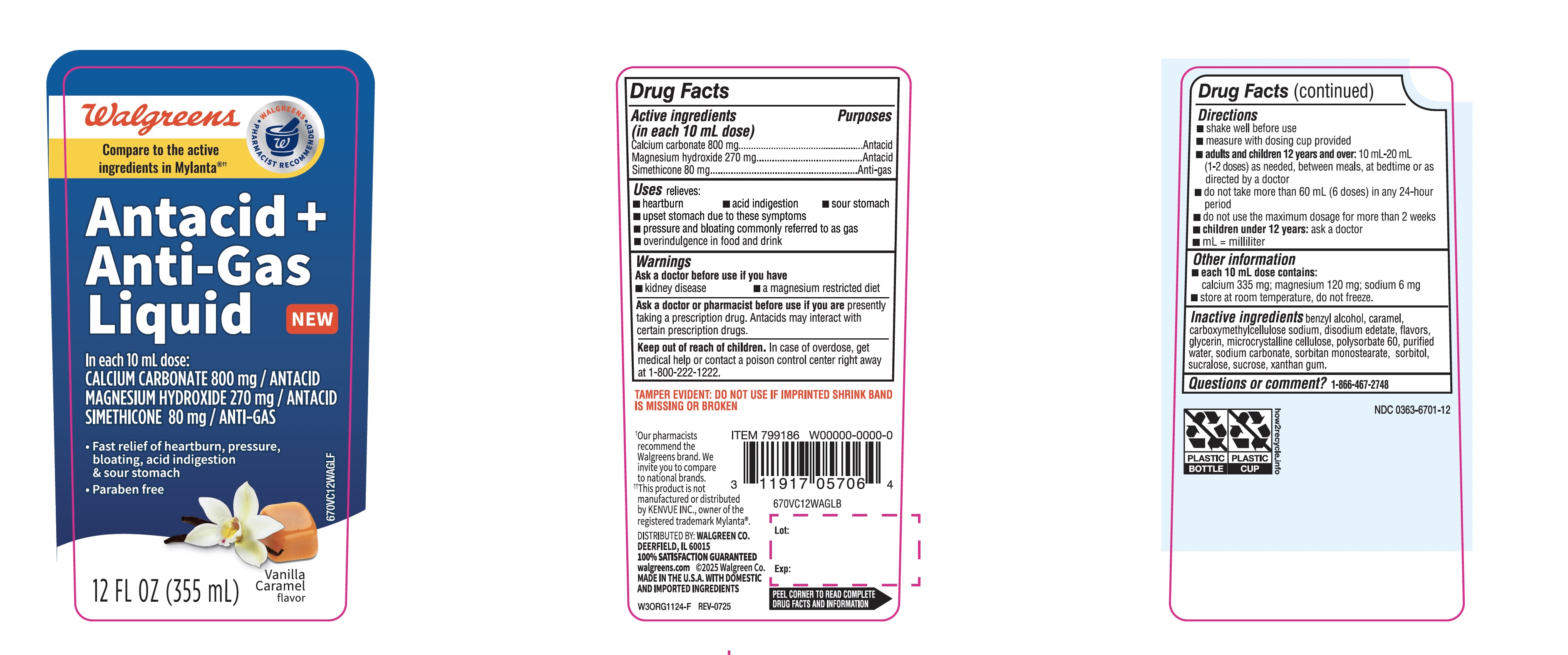 DRUG LABEL: Walgreen
NDC: 0363-6701 | Form: SUSPENSION
Manufacturer: WALGREENS CO.
Category: otc | Type: HUMAN OTC DRUG LABEL
Date: 20260116

ACTIVE INGREDIENTS: CALCIUM CARBONATE 800 mg/10 mL; MAGNESIUM HYDROXIDE 270 mg/10 mL; DIMETHICONE, UNSPECIFIED 80 mg/10 mL
INACTIVE INGREDIENTS: BENZYL ALCOHOL; CARAMEL; CARBOXYMETHYLCELLULOSE SODIUM, UNSPECIFIED; EDETATE DISODIUM; GLYCERIN; MICROCRYSTALLINE CELLULOSE; WATER; SODIUM CARBONATE; SORBITOL; SUCRALOSE; SUCROSE; XANTHAN GUM

Walgreen Liquid Antacid + Anti-Gas

Active ingredients (in each 10 mL dose)

Calcium carbonate 800 mg

Magnesium hydroxide 270 mg
Simethicone emulsion USP (equivalent to Simethicone) 80 mg

Purpose

Antacid

Antacid
Anti-gas

Uses

relieves:

- heartburn
- pressure and bloating commonly referred to as gas
- acid indigestion
- sour stomach
- upset stomach due to these symptoms
- overindulgence in food and drink

Warnings

Ask a doctor before use if you have

- kidney disease
- a magnesium restricted diet

Ask a doctor or pharmacist before use if you are

presently taking a prescription drug. Antacids may interact with certain prescription drugs.

Keep out of reach of children.

In case of overdose, get medical help or contact a poison control center right away at 1-800-222-1222

Directions

- shake well before use
- measure with dosing cup provided
- adults and children 12 years and over: 10 mL-20 mL (1-2 doses) as needed, between meals, at bedtime or as directed by a doctor
- do not take more than 60 mL (6 doses) in any 24- hour period
- do not use the maximum dosage for more than 2 weeks
- children under 12 years: ask a doctor
- mL= milliliter

Other information

- each 10 mL dose contains: calcium 335 mg; magnesium 120 mg; sodium 6 mg
- store at room temperature, do not freeze.

Inactive ingredients

benzyl alcohol, caramel, carboxymethylcellulose sodium, disodium edetate, flavors, glycerin, microcrystalline cellulose, purified water, sodium carbonate, sorbitol, sucralose, sucrose, xanthan gum

Questions or comment?

1-866-467-2748

Principal Display Panel

Compare to active ingredients in Mylanta®*

NDC 0363-6701-12

Liquid

Antacid + Anti-Gas

For fast relief of heartburn, acid indigestion, and painful gas

- Paraben Free
- Great Taste

Vanilla Caramel Flavor

12 FL OZ (355mL)

TAMPER-EVIDENT: DO NOT USE IF PRINTED SEAL UNDER CAP IS BROKEN OR MISSING

Distributed by:

*This product is not manufactured or distributed by Infirst Healthcare Inc., the distributor of Mylanta®